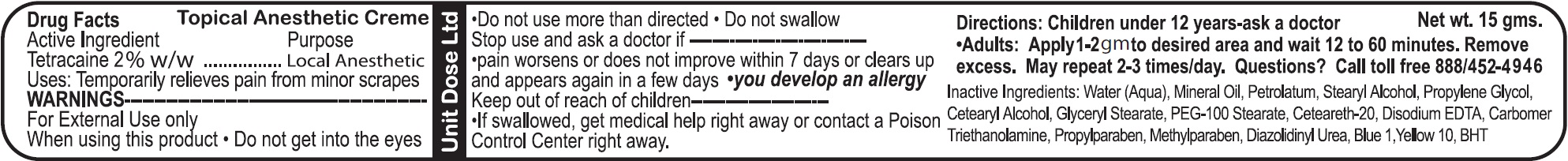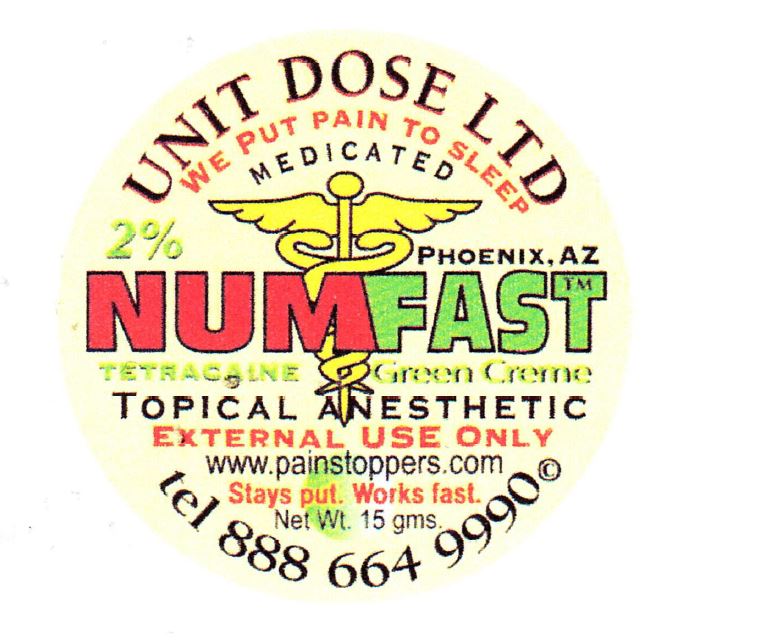 DRUG LABEL: Numfast Tetracaine Green
NDC: 67194-020 | Form: CREAM
Manufacturer: Unit Dose, Ltd.
Category: otc | Type: HUMAN OTC DRUG LABEL
Date: 20231019

ACTIVE INGREDIENTS: TETRACAINE 20 mg/1 g
INACTIVE INGREDIENTS: WATER; MINERAL OIL; PETROLATUM; STEARYL ALCOHOL; PROPYLENE GLYCOL; CETOSTEARYL ALCOHOL; GLYCERYL MONOSTEARATE; PEG-100 STEARATE; POLYOXYL 20 CETOSTEARYL ETHER; EDETATE DISODIUM; TROLAMINE; PROPYLPARABEN; METHYLPARABEN; DIAZOLIDINYL UREA; FD&C BLUE NO. 1; D&C YELLOW NO. 10; BUTYLATED HYDROXYTOLUENE

Numfast Tetracaine Green

Active Ingredient

Tetracaine 2% w/w

Purpose

Local Anesthetic

Uses:

Temporarily relieves pain from minor scrapes

WARNINGS

For External Use only

When using this product

- Do not get into the eyes
- Do not use more than directed
- Do not swallow

Stop use and ask a doctor if

- pain worsens or does not improve within 7 days or cleans up and appears again in a few days
- you develop an allergy

Keep out of reach of children

- If swallowed, get medical help right away or contact a Poison Control Center right away.

Directions:

Children under 12 years-ask a doctor

- Adults: Apply 1-2 gm to desired area and wait 12 to 60 minutes. Remove excess. May repeat 2-3 times/day.

Questions?

Call toll free 888/452-4946

Inactive Ingredients:

Water (Aqua), Mineral Oil, Petrolatum, Stearyl Alcohol, Propylene Glycol, Cetearyl Alcohol, Glyceryl Stearate, PEG-100 Stearate, Ceteareth-20, Disodium EDTA, Carbomer, Triethanolamine, Propylparaben, Methylparaben, Diazolidinyl Urea, Blue 1, Yellow 10, BHT